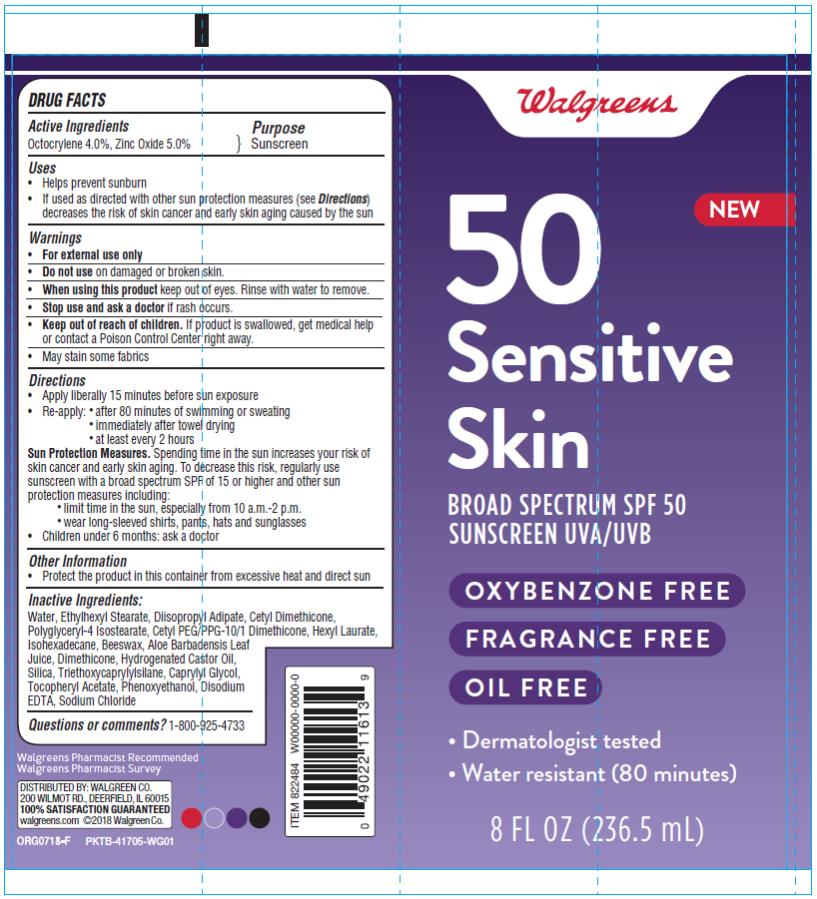 DRUG LABEL: Sensitive Skin 8 oz
NDC: 0363-8224 | Form: LOTION
Manufacturer: Walgreen Company
Category: otc | Type: HUMAN OTC DRUG LABEL
Date: 20180917

ACTIVE INGREDIENTS: OCTOCRYLENE 4 mg/100 mL; ZINC OXIDE 5 mg/100 mL
INACTIVE INGREDIENTS: WATER; ETHYLHEXYL STEARATE; DIISOPROPYL ADIPATE; HEXYL LAURATE; ISOHEXADECANE; YELLOW WAX; ALOE VERA LEAF; DIMETHICONE; HYDROGENATED CASTOR OIL; SILICON DIOXIDE; TRIETHOXYCAPRYLYLSILANE; CAPRYLYL GLYCOL; PHENOXYETHANOL; EDETATE DISODIUM ANHYDROUS; SODIUM CHLORIDE

Sensitive Skin 8 oz

Walgreens Sensitive Skin Sunscreen Lotion

Active Ingredients

Octocrylene 4.0%, Zinc Oxide 5.0%

Purpose

Sunscreen

Uses

- helps prevent sunburn
- if used as directed with other sun protection measures (see Directions), decreases the risk of skin cancer and early skin aging caused by the sun

Warnings

For external use only

Do not use

on damaged or broken skin

When using this product

keep out of eyes. Rinse with water to remove.

Stop use and ask a doctor

if rash occurs

Keep out of reach of children.

If swallowed, get medical help or contact a Poison Control Center right away.

May stain some fabrics

Directions

- apply liberally 15 minutes before sun exposure
- reapply:
  • after 80 minutes of swimming or sweating
  • immediately after towel drying
  • at least every 2 hours
- Sun Protection Measures. Spending time in the sun increases your risk of skin cancer and early skin aging. To decrease this risk, regularly use a sunscreen with a Broad Spectrum SPF of 15 or higher and other sun protection measures including:
  • limit time in the sun, especially from 10 a.m. - 2 p.m.
  • wear long-sleeve shirts, pants, hats, and sunglasses
- children under 6 months: Ask a doctor

Inactive Ingredients

Deionized Water, Ethylhexyl Stearate, Disopropyl Adipate, Cetyl Dimethicone, Polyglycery-4 Isosteate, Cetyl PEG/PPG-10/1 Dimethicone, Hexyl Laurate, Isohexadecane, Beeswax, Aloe Barbadensis Leaf Juice, Dimethicone, Hydrogenated Castor Oil, Silica, Triethoxycaprylylsilane, Caprylyl Glycol, Tocopherol Acetate, Phenoxyethanol, Disodium EDTA, Sodium Chloride

Other Information

- Protect the product in this container from excessive heat and direct sun
- Store at room temperature

Questions or comments?

www.walgreens.com or call toll free 1-800-925-4733

PRINCIPAL DISPLAY PANEL

50
Sensitive Skin
Broad spectrum SPF 50
Sunscreen UVA/UVB
Oxybenzone Free

Fragrance Free

Oil Free

Dermatologist test

Water Resistant (80 minutes)
8 FL OZ (236.5 mL)